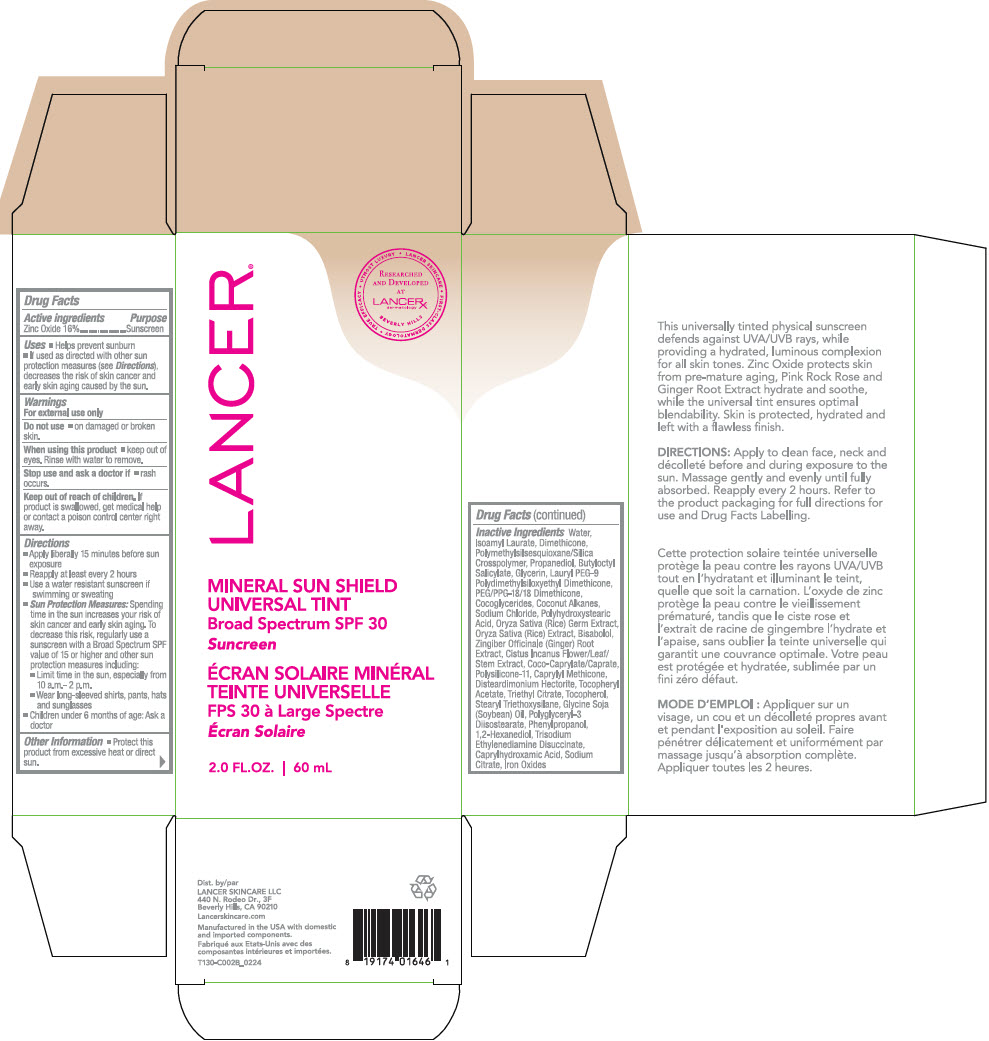 DRUG LABEL: Lancer Mineral Sun Shield Universal Tint Broadspectrum SPF 30
NDC: 72704-130 | Form: CREAM
Manufacturer: Lancer Skincare LLC
Category: otc | Type: HUMAN OTC DRUG LABEL
Date: 20250513

ACTIVE INGREDIENTS: Zinc Oxide 16 mg/100 mL
INACTIVE INGREDIENTS: water; Isoamyl Laurate; Dimethicone; Propanediol; Butyloctyl Salicylate; Glycerin; Lauryl PEG-9 Polydimethylsiloxyethyl Dimethicone; PEG/PPG-18/18 Dimethicone; COCO-GLYCERIDES; COCONUT ALKANES; Sodium Chloride; POLYHYDROXYSTEARIC ACID (2300 MW); Rice Germ; LEVOMENOL; Ginger; CISTUS INCANUS FLOWERING TOP; COCOYL CAPRYLOCAPRATE; DIMETHICONE/VINYL DIMETHICONE CROSSPOLYMER (SOFT PARTICLE); CAPRYLYL TRISILOXANE; DISTEARDIMONIUM HECTORITE; .ALPHA.-TOCOPHEROL ACETATE; Triethyl Citrate; Tocopherol; STEARYL TRIETHOXYSILANE; Soybean Oil; Polyglyceryl-3 Diisostearate; Phenylpropanol; 1,2-Hexanediol; Trisodium Ethylenediamine Disuccinate; Caprylhydroxamic Acid; SODIUM CITRATE, UNSPECIFIED FORM; FERROSOFERRIC OXIDE; FERRIC OXIDE RED; FERRIC OXIDE YELLOW

Lancer® Mineral Sun Shield Universal Tint Broadspectrum SPF 30

Drug Facts

Active ingredients

Zinc Oxide 16%

Purpose

Sunscreen

Uses

- Helps prevent sunburn
- If used as directed with other sun protection measures (see Directions), decreases the risk of skin cancer and early skin aging caused by the sun.

Warnings

For external use only

Do not use

- on damaged or broken skin.

When using this product

- keep out of eyes. Rinse with water to remove.

Stop use and ask a doctor if

- rash occurs.

Keep out of reach of children. If product is swallowed, get medical help or contact a poison control center right away.

Directions

- Apply liberally 15 minutes before sun exposure
- Reapply at least every 2 hours
- Use a water resistant sunscreen if swimming or sweating
- Sun Protection Measures: Spending time in the sun increases your risk of skin cancer and early skin aging. To decrease this risk, regularly use a sunscreen with a Broad Spectrum SPF value of 15 or higher and other sun protection measures including:
  - Limit time in the sun, especially from 10 a.m.-2 p.m.
  - Wear long-sleeved shirts, pants, hats and sunglasses
- Children under 6 months of age: Ask a doctor

Other Information

- Protect this product from excessive heat or direct sun.

Inactive Ingredients

Water, Isoamyl Laurate, Dimethicone, Polymethylsilsesquioxane/Silica Crosspolymer, Propanediol, Butyloctyl Salicylate, Glycerin, Lauryl PEG-9 Polydimethylsiloxyethyl Dimethicone, PEG/PPG-18/18 Dimethicone, Cocoglycerides, Coconut Alkanes, Sodium Chloride, Polyhydroxystearic Acid, Oryza Sativa (Rice) Extract, Bisabolol, Zingiber Officinale (Ginger) Root Extract, Cistus Incanus Flower/Leaf/Stem Extract, Coco-Caprylate/Caprate, Polysilicone-11, Caprylyl Methicone, Disteardimonium Hectorite, Tocopheryl Acetate, Triethyl Citrate, Tocopherol, Stearyl Triethoxysilane, Glycine Soja (Soybean) Oil, Polyglyceryl-3 Diisostearate, Phenylpropanol, 1,2-Hexanediol, Trisodium Ethylenediamine Disuccinate, Caprylhydroxamic Acid, Sodium Citrate, Iron Oxides

Dist. by
LANCER SKINCARE LLC
440 N. Rodeo Dr., 3F
Beverly Hills, CA 90210

PRINCIPAL DISPLAY PANEL - 60 mL Bottle Carton

LANCER®

• UTMOST LUXURY
• LANCER SKINCARE
• FIRST-CLASS DERMATOLOGY
• TRUE EFFICACY

RESEARCHED
AND DEVELOPED
AT
LANCERX™
dermatology

BEVERLY HILLS

MINERAL SUN SHIELD
UNIVERSAL TINT
Broad Spectrum SPF 30
Sunscreen

2.0 FL.OZ. | 60 mL